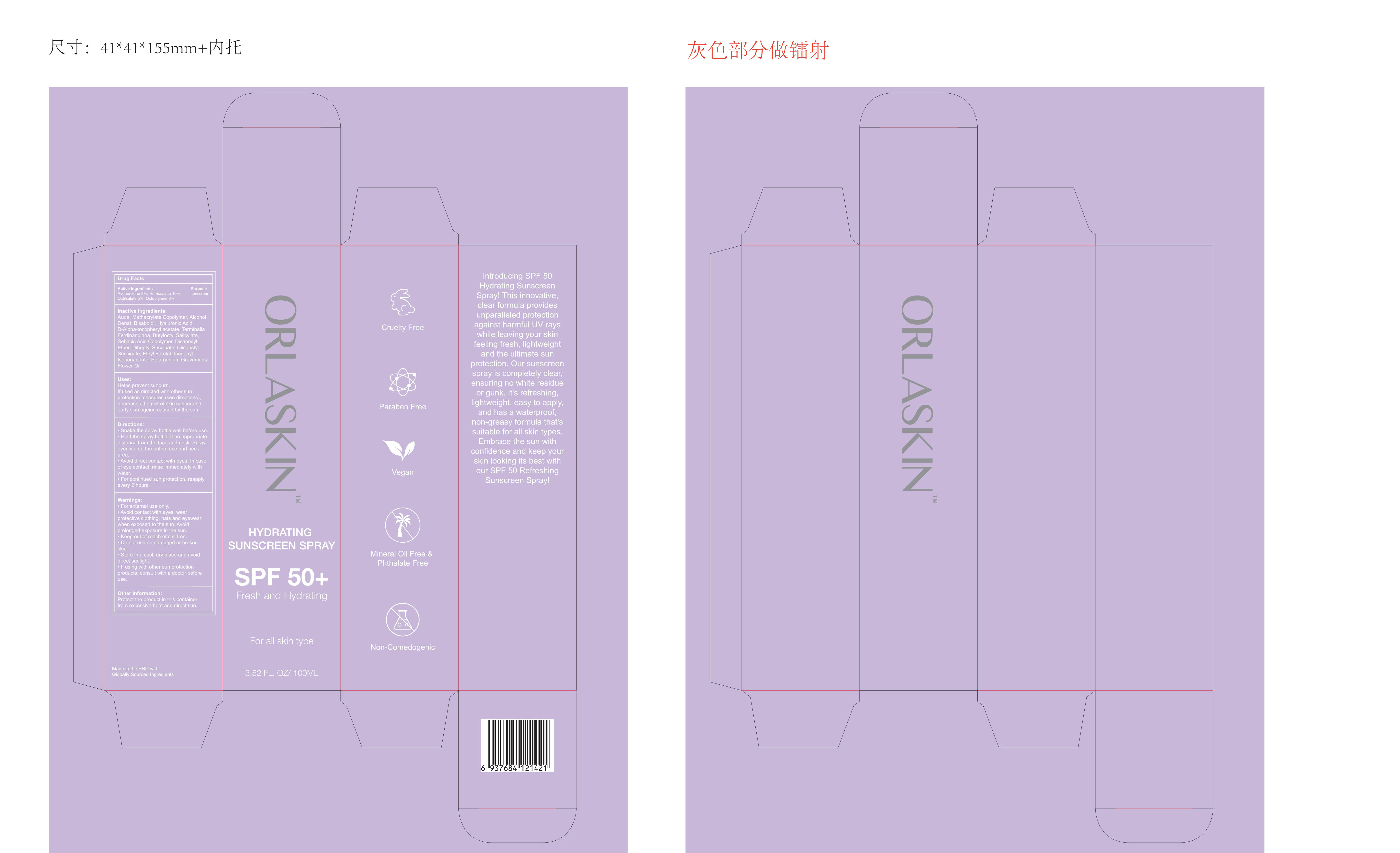 DRUG LABEL: ORLASKIN HYDRATING SUNSCREEN
NDC: 83447-003 | Form: SPRAY
Manufacturer: Guangzhou Fantesy Biotechnology Co.,Ltd
Category: otc | Type: HUMAN OTC DRUG LABEL
Date: 20260105

ACTIVE INGREDIENTS: OCTOCRYLENE 8 g/100 mL; HOMOSALATE 10 g/100 mL; OCTISALATE 5 g/100 mL; AVOBENZONE 3 g/100 mL
INACTIVE INGREDIENTS: HYALURONIC ACID; .ALPHA.-TOCOPHEROL ACETATE; KAKADU PLUM; BUTYLOCTYL SALICYLATE; CAPRYLOYL GLYCERIN/SEBACIC ACID COPOLYMER (2000 MPA.S); WATER; ETHYL ACRYLATE AND METHYL METHACRYLATE COPOLYMER (2:1; 750000 MW); ALCOHOL; LEVOMENOL; DICAPRYLYL ETHER; DIHEPTYL SUCCINATE; ETHYL FERULATE; ISONONYL ISONONANOATE; PELARGONIUM GRAVEOLENS FLOWER OIL; DOCUSATE SODIUM

83447-003

ACTIVE INGREDIENT

Homosalate 10%

Octocrylene 8%

Octilsalate 5%

Avobenzone 3%

PURPOSE

sunscreen

Uses

Helps prevent sunburn.

If used as directed with other sun protection measures (see directions), decreases the risk of skin cancer and early skin ageing caused by the sun.

Warnings

For external use only.

Avoid contact with eyes , wear protective clothing , hats and eyewear when exposed to the sun . Avoid prolonged exposure in the sun.

Keep out of reach of children.

Do not use on damaged or brokenskin.

Store in a cool , dry place and avoiddirect sunlight.

If using with other sun protection products , consult with a doctor before use.

Do not use on damaged or broken skin

Keep out of reach of children

Directions

Shake the spray bottle well before use.

Hold the spray bottle at an appropriate distance from the face and neck . Spray evenly onto the entire face and neck area.

Avoid direct contact with eves . In case of eye contact , rinse immediately with water.

For continued sun protection , reapply every 2 hours

Other information

Protect the product in this container from excessive heat and direct sun

Inactive Ingredients

Auqa , Methacrylate Copolymer , Alcohol Denat , Bisabolol , Hvaluronic Acid, D-alpha-tocopheryl acetate , Terminalia Ferdinandiana , Butyloctyl Salicylate, Sebacic Acid Copolymer , Dicaprylyl Ether , Diheptyl Succinate , Diisooctyl Succinate , Ethyl Ferulat , Isononyl sononanoate , Pelargonium Graveolens Flower Oil